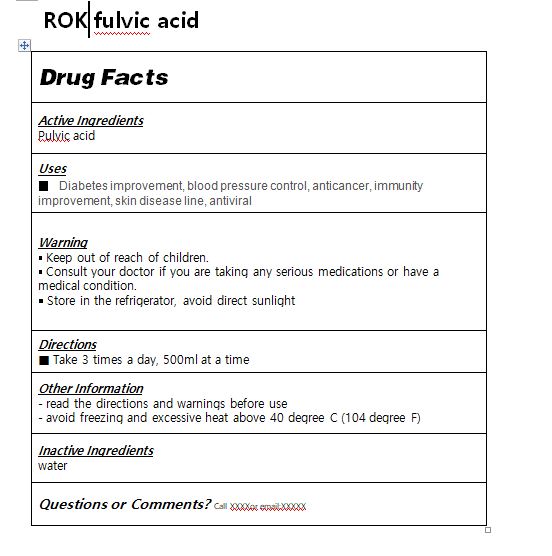 DRUG LABEL: ROK fulvic acid
NDC: 82236-0003 | Form: LIQUID
Manufacturer: Waterrok Co., Ltd.
Category: otc | Type: HUMAN OTC DRUG LABEL
Date: 20211117

ACTIVE INGREDIENTS: FULVIC ACID 1.45 g/1000 mL
INACTIVE INGREDIENTS: WATER

Drug Facts

ACTIVE INGREDIENT

pulvic acid

PURPOSE

Diabetes improvement, blood pressure control, anticancer, immunity improvement, skin disease line, antiviral

KEEP OUT OF REACH OF THE CHILDREN

INDICATIONS AND USAGE

Take 3 times a day, 500ml at a time

▪ Keep out of reach of children.

▪ Consult your doctor if you are taking any serious medications or have a medical condition.

￭ Store in the refrigerator, avoid direct sunlight

DOSAGE AND ADMINISTRATION

oral use only

INACTIVE INGREDIENT

Water